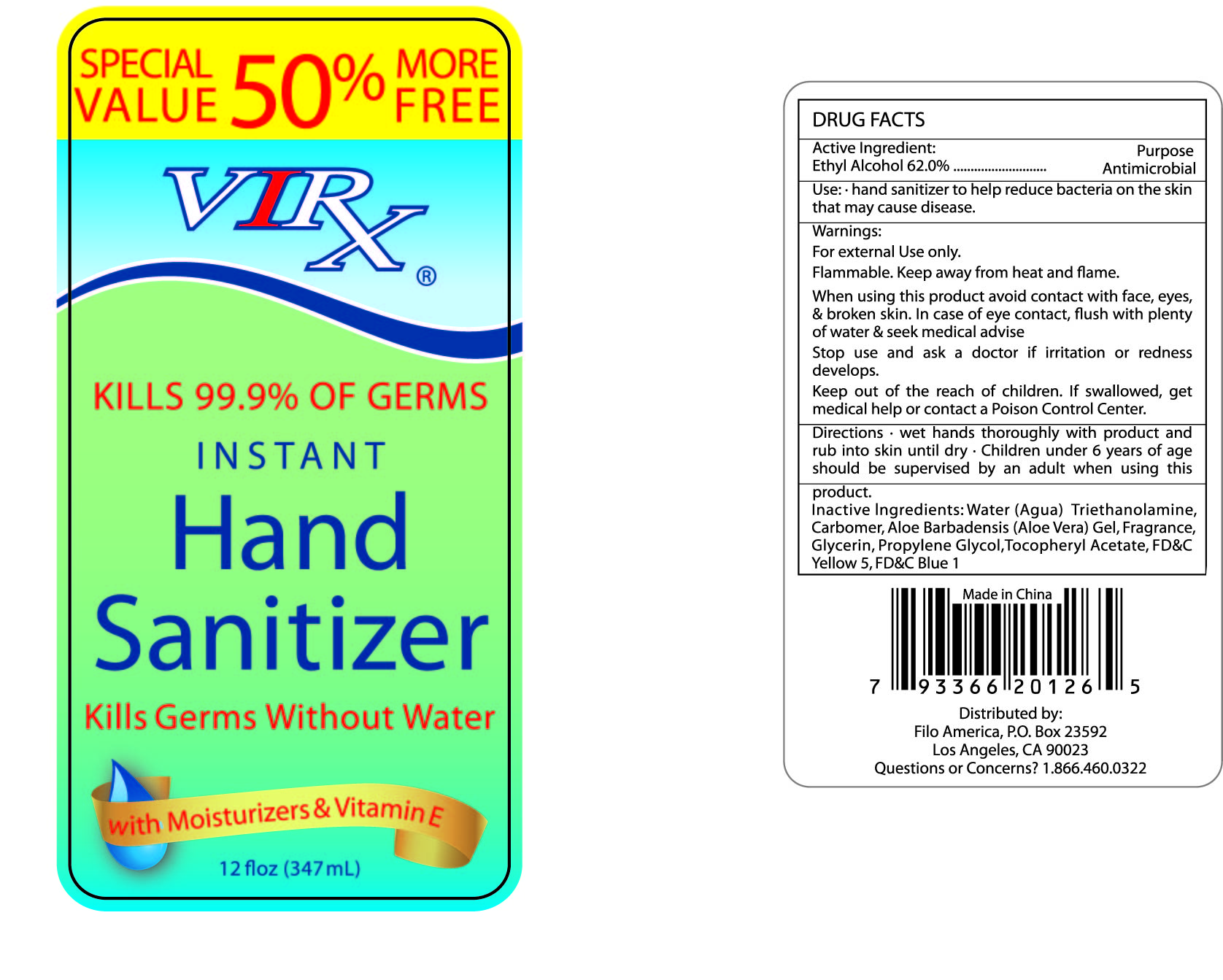 DRUG LABEL: Virx Instant Hand Sanitizer with moisturizers and Vitamin E
NDC: 50438-100 | Form: GEL
Manufacturer: Filo America
Category: otc | Type: HUMAN OTC DRUG LABEL
Date: 20130731

ACTIVE INGREDIENTS: alcohol 62 mL/100 mL
INACTIVE INGREDIENTS: WATER; PROPYLENE GLYCOL; ALOE VERA LEAF; CARBOMER 934; GLYCERIN; .ALPHA.-TOCOPHEROL ACETATE, D-; TROLAMINE

Drug facts

Active ingredient Purpose

Alcohol 62% ... Antiseptic

PURPOSE

Hand sanitizer to help reduce bacteria on the skin that may cause disease.

KEEP OUT OF REACH OF CHILDREN

If swallowed, get medical help or contact local poison control center right away.

Children must be supervised in use of this product.

INDICATIONS AND USAGE

keep out of eyes

when water, soap and towel are not available

WARNINGS

For external use only.
Flammable. Keep away from hear or flame.

When using this products, avoid contact with face, eyes and broken skin. In case of contact, flush eyes with plenty of water and seek medical advise.

Stop using and ask a doctor, if irritation and redness develops, if condition persists for more than 72 hours, consult a doctor.

DOSAGE AND ADMINISTRATION

Wet hands thoroughly with product and rub the skin until dry.

INACTIVE INGREDIENT

Water, Carbomer, Glycerin, Propylene Glycol, Triethanolamine, Aloe Barbadensis Leaf Juice, Tocopheryl Acetate, Fragrance, FD and C Yellow 5, FD and C Blue 1